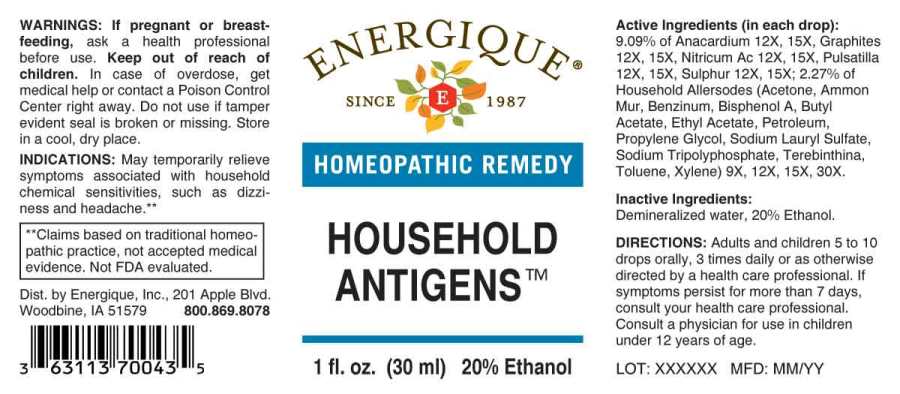 DRUG LABEL: Household Antigens
NDC: 44911-0536 | Form: LIQUID
Manufacturer: Energique, Inc.
Category: homeopathic | Type: HUMAN OTC DRUG LABEL
Date: 20240927

ACTIVE INGREDIENTS: ACETONE 9 [hp_X]/1 mL; SODIUM TRIPOLYPHOSPHATE 9 [hp_X]/1 mL; PROPYLENE GLYCOL 9 [hp_X]/1 mL; BENZENE 9 [hp_X]/1 mL; AMMONIUM CHLORIDE 9 [hp_X]/1 mL; SODIUM LAURYL SULFATE 9 [hp_X]/1 mL; TURPENTINE OIL 9 [hp_X]/1 mL; BUTYL ACETATE 9 [hp_X]/1 mL; ETHYL ACETATE 9 [hp_X]/1 mL; TOLUENE 9 [hp_X]/1 mL; XYLENE (MIXED ISOMERS) 9 [hp_X]/1 mL; BISPHENOL A 9 [hp_X]/1 mL; KEROSENE 9 [hp_X]/1 mL; SEMECARPUS ANACARDIUM JUICE 12 [hp_X]/1 mL; GRAPHITE 12 [hp_X]/1 mL; NITRIC ACID 12 [hp_X]/1 mL; ANEMONE PRATENSIS 12 [hp_X]/1 mL; SULFUR 12 [hp_X]/1 mL
INACTIVE INGREDIENTS: WATER; ALCOHOL

Drugs:

ACTIVE INGREDIENTS:

(in each drop): 9.09% of Anacardium Orientale 12X, 15X, Graphites 12X, 15X, Nitricum Acidum 12X, 15X, Pulsatilla (Pratensis) 12X, 15X, Sulphur 12X, 15X; 2.27% of Acetone 9X, 12X, 15X, 30X, Sodium Tripolyphosphate 9X, 12X, 15X, 30X, Propylene Glycol 9X, 12X, 15X, 30X, Benzinum 9X, 12X, 15X, 30X, Ammonium Muriaticum 9X, 12X, 15X, 30X, Sodium Lauryl Sulfate 9X, 12X, 15X, 30X, Terebinthina 9X, 12X, 15X, 30X, Butyl Acetate 9X, 12X, 15X, 30X, Ethyl Acetate 9X, 12X, 15X, 30X, Toluene 9X, 12X, 15X, 30X, Xylene 9X, 12X, 15X, 30X, Bisphenol A 9X, 12X, 15X, 30X, Petroleum 9X, 12X, 15X, 30X.

INDICATIONS:

May temporariy relieve symptoms associated with household chemicals sensitivities, such as dizziness and headache.**

**Claims based on traditional homeopathic practice, not accepted medical evidence. Not FDA evaluated.

WARNINGS:

If pregnant or breast-feeding, ask a health professional before use.

Keep out of reach of children. In case of overdose, get medical help or contact a Poison Control Center right away.

Do not use if tamper evident seal is broken or missing.

Store in a cool, dry place.

Keep out of reach of children. In case of overdose, get medical help or contact a Poison Control Center right away.

DIRECTIONS:

Adults and children 5 to 10 drops orally, 3 times daily or as otherwise directed by a health care porfessional. If symptoms persist for more than 7 days, consult your health care professional. Consult a physician for use in children under 12 years of age.

INDICATIONS:

May temporariy relieve symptoms associated with household chemicals sensitivities, such as dizziness and headache.**

**Claims based on traditional homeopathic practice, not accepted medical evidence. Not FDA evaluated.

INACTIVE INGREDIENTS:

Demineralized water, 20% Ethanol.

QUESTIONS:

Dist. by Energique, Inc.

201 Apple Blvd

Woodbine, IA 51579

800-869-8078

PACKAGE LABEL DISPLAY:

ENERGIQUE

since 1987

HOMEOPATHIC REMEDY

HOUSEHOLD ANTIGENS

1 fl. oz (30 ml)